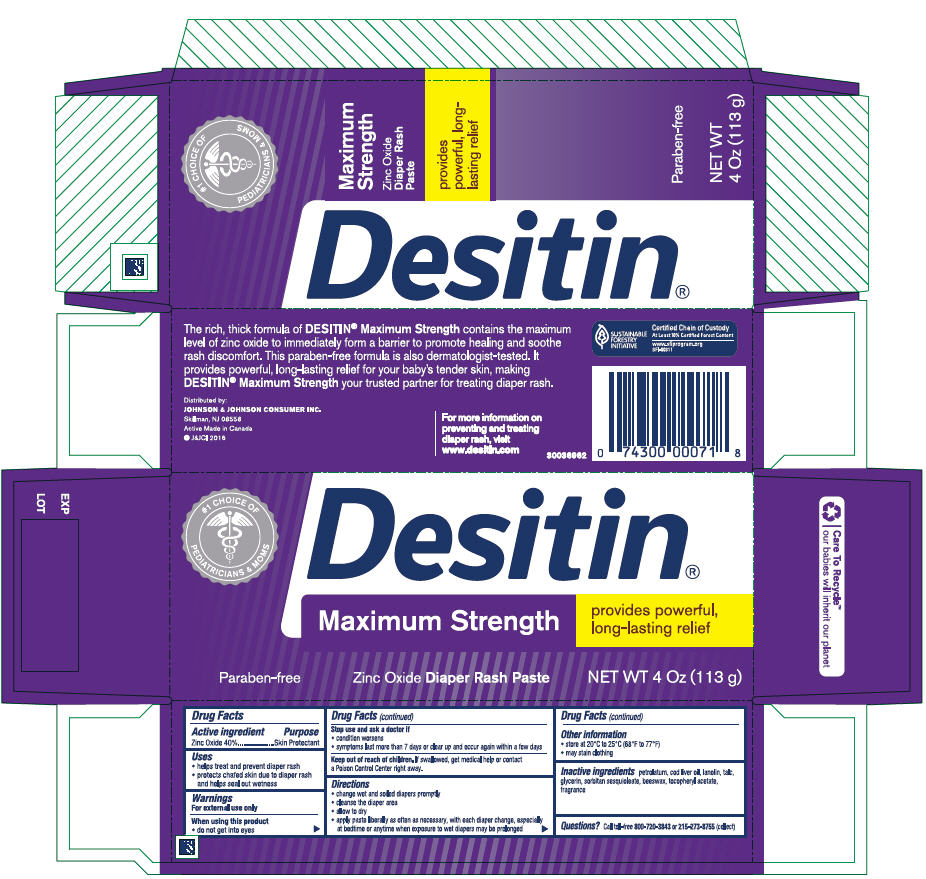 DRUG LABEL: Desitin Maximum Strength Diaper Rash
NDC: 69968-0061 | Form: PASTE
Manufacturer: Kenvue Brands LLC
Category: otc | Type: HUMAN OTC DRUG LABEL
Date: 20241115

ACTIVE INGREDIENTS: ZINC OXIDE 400 mg/1 g
INACTIVE INGREDIENTS: PETROLATUM; COD LIVER OIL; LANOLIN; TALC; GLYCERIN; SORBITAN SESQUIOLEATE; YELLOW WAX; .ALPHA.-TOCOPHEROL ACETATE

Desitin® Maximum Strength Diaper Rash Paste

Drug Facts

Active ingredient

Zinc Oxide 40%

Purpose

Skin Protectant

Uses

- helps treat and prevent diaper rash
- protects chafed skin due to diaper rash and helps seal out wetness

Warnings

For external use only

When using this product

- do not get into eyes

Stop use and ask a doctor if

- condition worsens
- symptoms last more than 7 days or clear up and occur again within a few days

Keep out of reach of children. If swallowed, get medical help or contact a Poison Control Center right away.

Directions

- change wet and soiled diapers promptly
- cleanse the diaper area
- allow to dry
- apply paste liberally as often as necessary, with each diaper change, especially at bedtime or anytime when exposure to wet diapers may be prolonged

Other information

- store at 20°C to 25°C (68°F to 77°F)
- may stain clothing

Inactive ingredients

petrolatum, cod liver oil, lanolin, talc, glycerin, sorbitan sesquioleate, beeswax, tocopheryl acetate, fragrance

Questions?

Call toll-free 800-720-3843 or 215-273-8755 (collect)

Distributed by:
JOHNSON & JOHNSON CONSUMER INC.
Skillman, NJ 08558

PRINCIPAL DISPLAY PANEL - 113 g Tube Carton

#1 CHOICE OF PEDIATRICIANS & MOMS

Desitin®
Maximum Strength

provides powerful,
long-lasting relief

• Paraben-free Zinc Oxide Diaper Rash Paste NET WT 4 Oz (113 g)